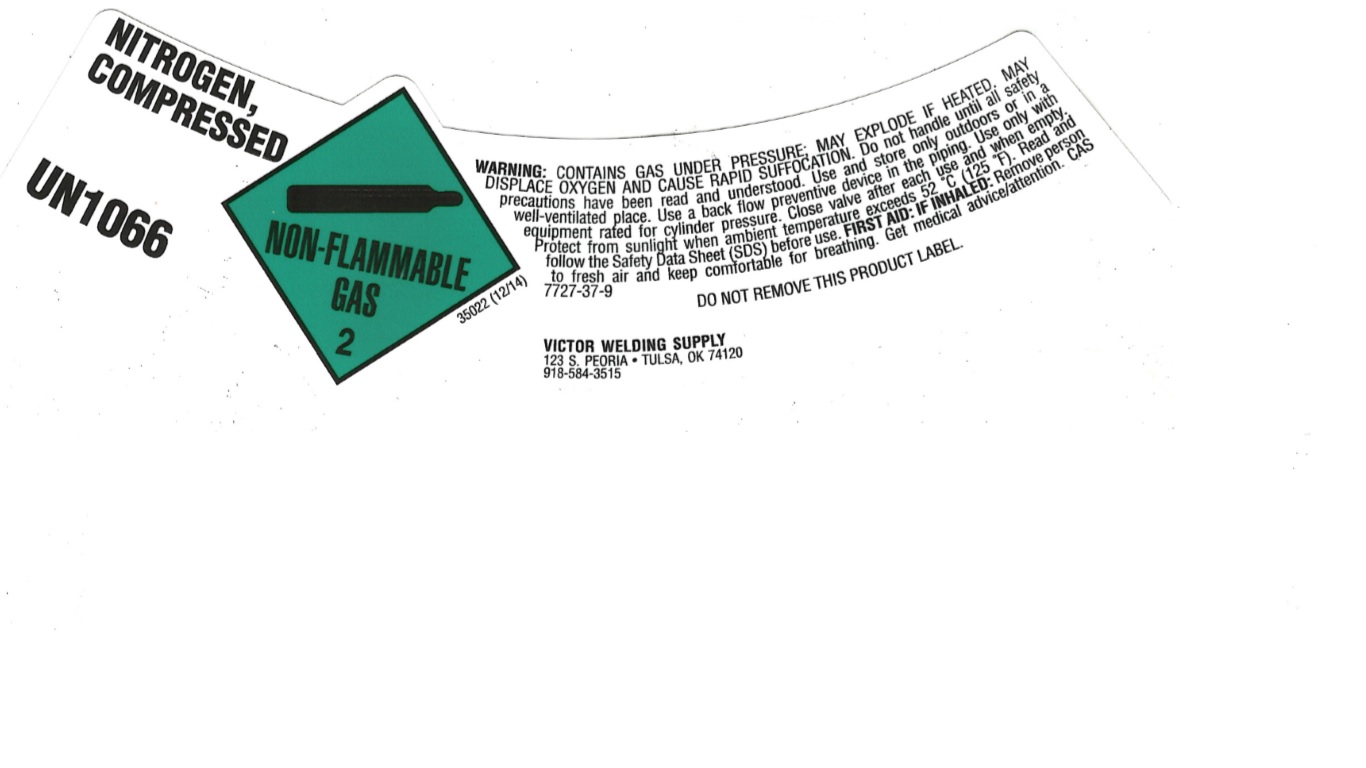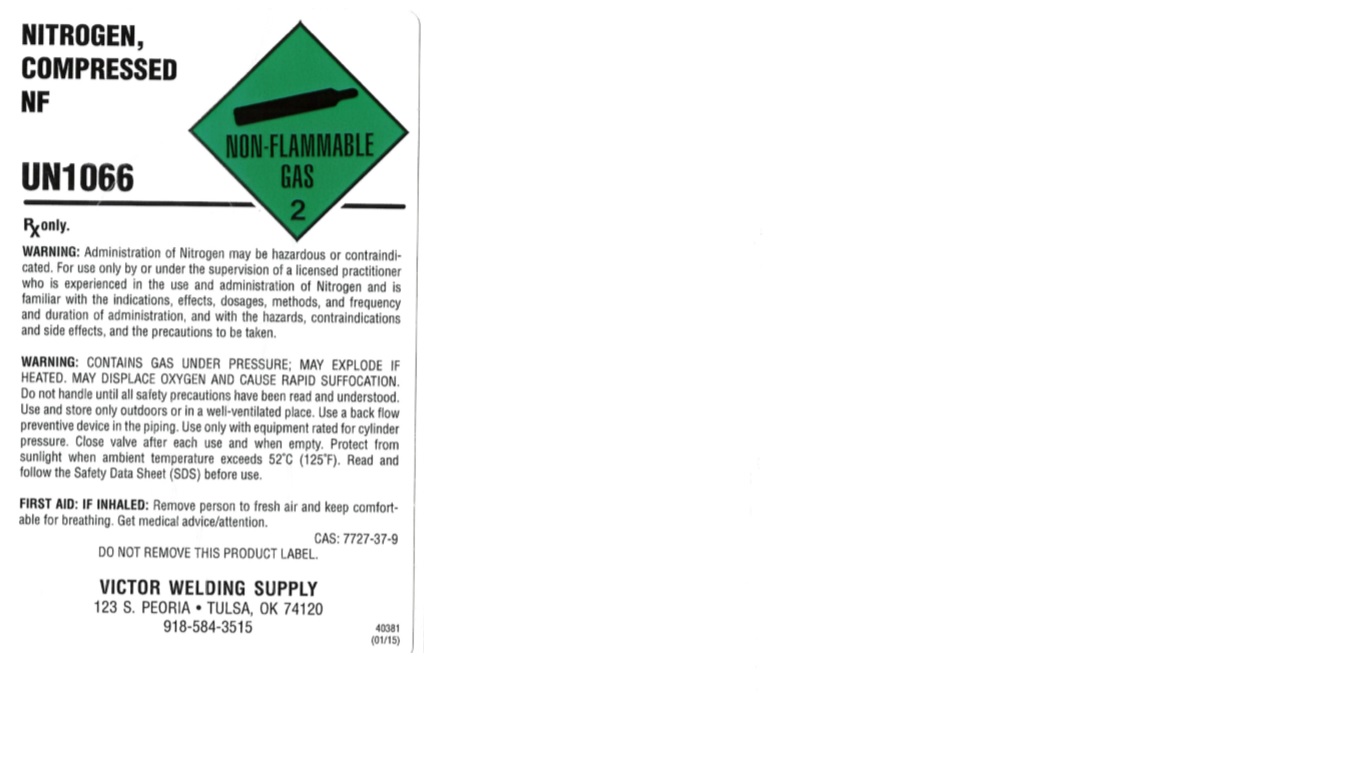 DRUG LABEL: Nitrogen
NDC: 66961-120 | Form: GAS
Manufacturer: Victor Welding Supply Company
Category: prescription | Type: HUMAN PRESCRIPTION DRUG LABEL
Date: 20251121

ACTIVE INGREDIENTS: NITROGEN 992 mL/1 L

Nitrogen Label

PACKAGE LABEL

NITROGEN, COMPRESSED
UN1066
WARNING: CONTAINS GAS UNDER PRESSURE; MAY EXPLODE IF HEATED. MAY DISPLACE OXYGEN AND CAUSE RAPID SUFFOCATION. Do not handle until all safety precautions have been read and understood. Use and store only outdoors or in a well-ventilated place. Use a back flow preventive device in the piping. Use only with equipment rated for cylinder pressure. Close valve after each use and when empty. Protect from sunlight when ambient temperature exceeds 52 C (125 F). Read and follow the Safety Data Sheet (SDS) before use. FIRST AID: IF INHALED: Remove person to fresh air and keep comfortable for breathing. Get medical advice/attention. CAS 7727-37-9
DO NOT REMOVE THIS PRODUCT LABEL.
VICTOR WELDING SUPPLY
123 S. PEORIA
TULSA, OK 74120
918-584-3515

PACKAGE LABEL

NITROGEN, COMPRESSED NF
UN1066
Rx only.
WARNING: Administration of Nitrogen may be hazardous or contraindicated. For use only by or under the supervision of a licensed practitioner who is experienced in the use and administration of Nitrogen and is familiar with the indications, effects, dosages, methods, and frequency and duration of administration, and with the hazards, contraindications and side effects, and the precautions to be taken.
WARNING: CONTAINS GAS UNDER PRESSURE; MAY EXPLODE IF HEATED. MAY DISPLACE OXYGEN AND CAUSE RAPID SUFFOCATION. Do not handle until all safety precautions have been read and understood. Use and store only outdoors or in a well-ventilated place. Use a back flow preventive device in the piping. Use only with equipment rated for cylinder pressure. Close valve after each use and when empty. Protect from sunlight when ambient temperature exceeds 52 C (125 F). Read and follow the Safety Data Sheet (SDS) before use.
FIRST AID: IF INHALED: Remove person to fresh air and keep comfortable for breathing. Get medical advice/attention.
CAS: 7727-37-9
DO NOT REMOVE THIS PRODUCT LABEL.
VICTOR WELDING SUPPLY
123 S. PEORIA
TULSA, OK 74120
918-584-3515